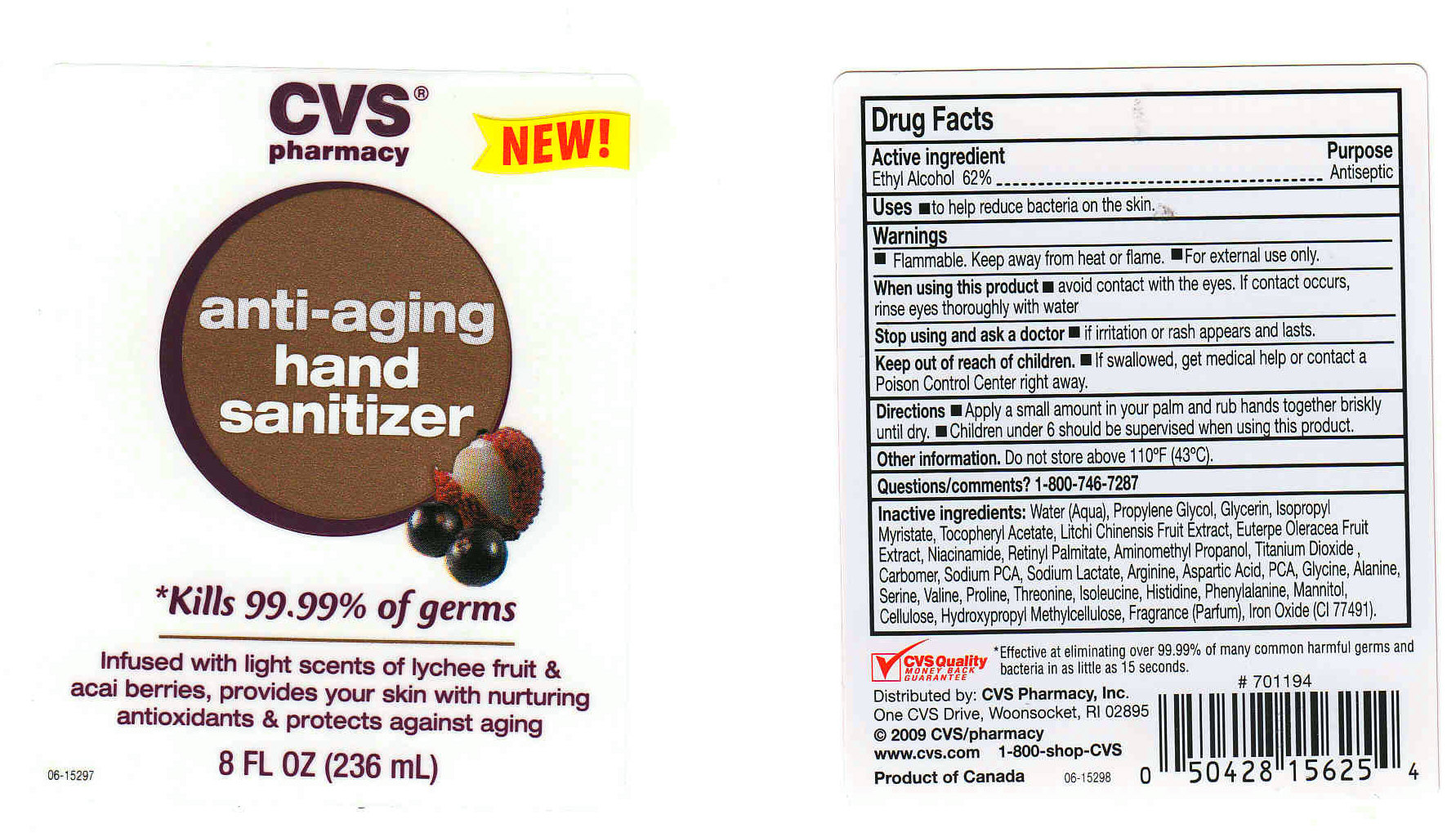 DRUG LABEL: CVS PHARMACY
NDC: 63148-251 | Form: GEL
Manufacturer: Apollo Health and Beauty Care
Category: otc | Type: HUMAN OTC DRUG LABEL
Date: 20091020

ACTIVE INGREDIENTS: ALCOHOL 62 mL/100 mL
INACTIVE INGREDIENTS: WATER 35.5780 mL/100 mL; PROPYLENE GLYCOL 1.0 mL/100 mL; GLYCERIN 0.2 mL/100 mL; ISOPROPYL MYRISTATE 0.01 mL/100 mL; ALPHA-TOCOPHEROL ACETATE 0.01 mL/100 mL; NIACINAMIDE 0.25 mL/100 mL; VITAMIN A PALMITATE 0.001 mL/100 mL; 2-AMINO-2-METHYL-1-PROPANOL 0.2 mL/100 mL; TITANIUM DIOXIDE 0.01 mL/100 mL; CARBOMER HOMOPOLYMER TYPE C 0.55 mL/100 mL; SODIUM PYRROLIDONE CARBOXYLATE 0.01 mL/100 mL; SODIUM LACTATE 0.01 mL/100 mL; ARGININE 0.01 mL/100 mL; ASPARTIC ACID 0.01 mL/100 mL; GLYCINE 0.01 mL/100 mL; ALANINE 0.01 mL/100 mL; SERINE 0.01 mL/100 mL; VALINE 0.01 mL/100 mL; PROLINE 0.01 mL/100 mL; THREONINE 0.01 mL/100 mL; ISOLEUCINE 0.01 mL/100 mL; HISTIDINE 0.01 mL/100 mL; PHENYLALANINE 0.01 mL/100 mL; MANNITOL 0.02 mL/100 mL; POWDERED CELLULOSE 0.02 mL/100 mL; HYPROMELLOSE 0.02 mL/100 mL; FERRIC OXIDE RED 0.001 mL/100 mL

CVS PHARMACY ANTI-AGING HAND SANITIZER

ACTIVE INGREDIENT

ETHYL ALCOHOL 62% (ANTISEPTIC)

USES

TO HELP REDUCE BACTERIA ON THE SKIN

WARNINGS

- FOR EXTERNAL USE ONLY.
- FLAMMABLE. KEEP AWAY FROM FIRE OR FLAME.

WHEN USING THIS PRODUCT

AVOID CONTACT WITH EYES. IF CONTACT OCCURS, RINSE WITH WATER.

STOP USE AND ASK A DOCTOR IF

IRRITATION OR RASH APPEARS AND LASTS.

KEEP OUT OF REACH OF CHILDREN

IN CASE OF ACCIDENTAL INGESTION, GET MEDICAL HELP OR CONTACT A POISON CONTROL CENTER IMMEDIATELY.

QUESTIONS/COMMENTS?:

1-800-746-7287

OTHER INFORMATION

DO NOT STORE ABOVE 110^0F (43^0C).

PACKAGE FRONT AND BACK LABELS

- (MM1): Labels8.jpg